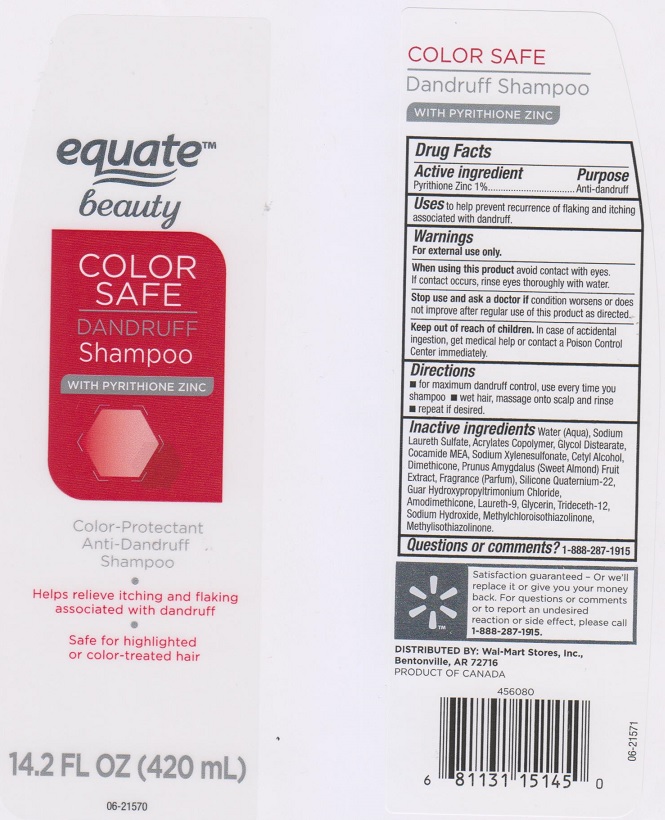 DRUG LABEL: Equate Beauty Color Safe Dandruff
NDC: 49035-437 | Form: SHAMPOO
Manufacturer: Wal-Mart Store Inc
Category: otc | Type: HUMAN OTC DRUG LABEL
Date: 20161219

ACTIVE INGREDIENTS: PYRITHIONE ZINC 10 mg/1 mL
INACTIVE INGREDIENTS: WATER; SODIUM LAURETH SULFATE; METHACRYLIC ACID - METHYL METHACRYLATE COPOLYMER (1:1); GLYCOL DISTEARATE; COCO MONOETHANOLAMIDE; SODIUM XYLENESULFONATE; CETYL ALCOHOL; DIMETHICONE; ALMOND OIL; QUATERNIUM-22; GUAR HYDROXYPROPYLTRIMONIUM CHLORIDE (1.7 SUBSTITUENTS PER SACCHARIDE); AMODIMETHICONE (3500 CST); POLIDOCANOL; GLYCERIN; TRIDECETH-12; SODIUM HYDROXIDE; METHYLCHLOROISOTHIAZOLINONE; METHYLISOTHIAZOLINONE

Drug Facts

Active ingredient

Pyrithione Zinc 1%

Purpose

Anti-dandruff

Uses

to help prevent recurrence of flaking and itching associated with dandruff.

Warnings

For external use only.

When using this product

avoid contact with eyes. If contact occurs, rinse eyes thoroughly with water.

Stop use and ask a doctor if

condition worsens or does not improve after regular use of this product as directed.

Keep out of reach of children.

In case of accidental ingestion, get medical help or contact a Poison Control Center immediately.

Directions

- for maximum dandruff control, use every time you shampoo.
- wet hair, massage onto scalp and rinse.
- repeat if desired.

Inactive ingredients

Water (Aqua), Sodium Laureth Sulfate, Acrylates Copolymer, Glycol Distearate, Cocamide MEA, Sodium Xylenesulfonate, Cetyl Alcohol, Dimethicone, Prunus Amygdalus (Sweet Almond) Fruit Extract, Fragrance (Parfum), Silicone Quaternium-22, Guar Hydroxypropyltrimonium Chloride, Amodimethicone, Laureth-9, Glycerin, Trideceth-12, Sodium Hydroxide, Methylchloroisothiazolinone, Methylisothiazolinone.

Questions or comments?

1-888-287-1915